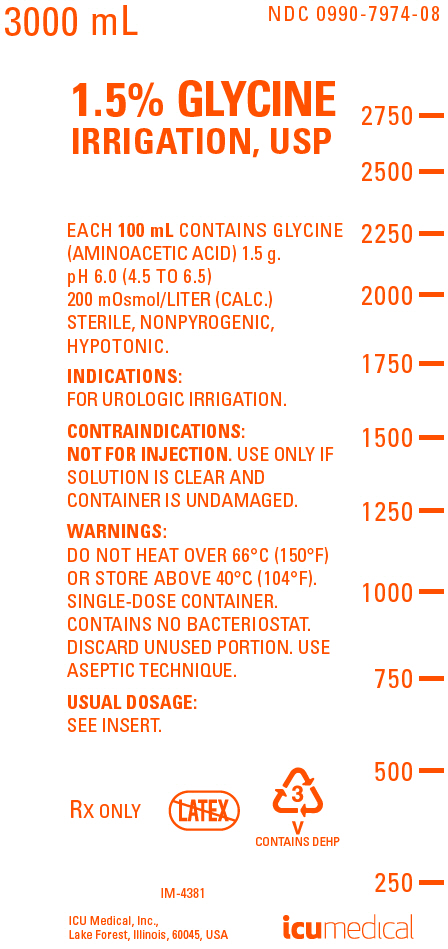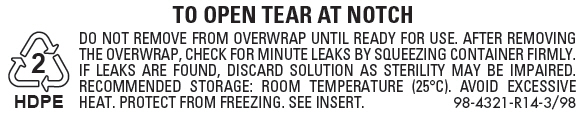 DRUG LABEL: Glycine
NDC: 0990-7974 | Form: IRRIGANT
Manufacturer: ICU Medical Inc.
Category: prescription | Type: HUMAN PRESCRIPTION DRUG LABEL
Date: 20251021

ACTIVE INGREDIENTS: GLYCINE 1.5 g/100 mL
INACTIVE INGREDIENTS: WATER

1.5% GLYCINE IRRIGATION, USP

NONELECTROLYTE IRRIGATING FLUID FOR TRANSURETHRAL SURGICAL PROCEDURES.

For Urologic Irrigation Only; Not For Injection By Usual Parenteral Routes

Flexible Irrigation Container

Rx only

DESCRIPTION

1.5% Glycine Irrigation, USP is a sterile, nonpyrogenic, hypotonic, aqueous solution of glycine intended only for urologic irrigation during transurethral surgical procedures.

Each 100 mL contains 1.5 g of glycine in water for injection. The solution is nonelectrolytic, hypotonic and has an osmolarity of 200 mOsmol/liter (calc.); pH 6.0 (4.5 to 6.5).

The solution contains no bacteriostat, antimicrobial agent or added buffer and is intended only for use as a single-dose irrigation. When smaller volumes are required, the unused portion should be discarded.

1.5% Glycine Irrigation is a urologic nonelectrolyte irrigant.

Glycine, USP is chemically designated aminoacetic acid (C2H5NO2), a white crystalline powder freely soluble in water. It has the following structural formula:

NH2CH2COOH

Water for Injection, USP is chemically designated H20.

The flexible plastic container is fabricated from a specially formulated polyvinylchloride. Water can permeate from inside the container into the overwrap but not in amounts sufficient to affect the solution significantly.

The semi-rigid container is fabricated from a specially formulated polyolefin. It is a copolymer of ethylene and propylene. The container requires no vapor barrier to maintain the proper drug concentration.

The flexible plastic container is fabricated from a specially formulated polyvinylchloride. Water can permeate from inside the container into the overwrap but not in amounts sufficient to affect the solution significantly. Solutions in contact with the plastic container may leach out certain chemical components from the plastic in very small amounts; however, biological testing was supportive of the safety of the plastic container materials. Exposure to temperatures above 25°C/77°F during transport and storage will lead to minor losses in moisture content. Higher temperatures lead to greater losses. It is unlikely that these minor losses will lead to clinically significant changes within the expiration period.

CLINICAL PHARMACOLOGY

Glycine is an amino acid and a nonelectrolyte. A solution of glycine in water is therefore nonconductive and suitable for urologic irrigation during electrosurgical procedures. A 1.5% concentration of glycine in water (200 mOsmol/liter calc.) is sufficient to minimize the risk of intravascular hemolysis which can occur from absorption of plain water through open prostatic veins during transurethral resection (TUR). It is hypotonic in relation to the extracellular fluid (280 mOsmol/liter). Any solution absorbed intravascularly during transurethral prostatic or bladder surgery, although variable in amount depending primarily on the extent of surgery, will be excreted by the kidney. Studies have shown that the absorption of glycine does not cause significant hemolysis (increase of free hemoglobin) or release significant amounts of free ammonia in the blood. Glycine is rapidly degraded in the liver by glycine oxidase.

Water is an essential constituent of all body tissues and accounts for approximately 70% of total body weight. Average normal adult daily requirement ranges from two to three liters (1.0 to 1.5 liters each for insensible water loss by perspiration and urine production).

Water balance is maintained by various regulatory mechanisms. Water distribution depends primarily on the concentration of electrolytes in the body compartments and sodium (Na^+) plays a major role in maintaining physiologic equilibrium.

INDICATIONS AND USAGE

1.5% Glycine Irrigation, USP is indicated for use as irrigating fluid during transurethral prostatic resection and other transurethral surgical procedures.

CONTRAINDICATIONS

NOT FOR INJECTION BY USUAL PARENTERAL ROUTES.

Do not use in patients with anuria.

WARNINGS

FOR UROLOGIC IRRIGATION ONLY.

Solutions for urologic irrigation must be used with caution in patients with severe cardiopulmonary or renal dysfunction. Irrigating fluids used during transurethral prostatectomy have been demonstrated to enter the systemic circulation in relatively large volumes. Thus, glycine irrigating solution must be regarded as a systemic drug. Absorption of large amounts of fluids containing glycine may significantly alter cardiopulmonary and renal dynamics.

Do not heat container over 66°C (150°F).

PRECAUTIONS

Cardiovascular status, especially of the patient with cardiac disease, should be carefully observed before and during transurethral resection of the prostate when using glycine irrigating solution, because the quantity of fluid absorbed into the systemic circulation by opened prostatic veins may produce significant expansion of the extracellular fluid and lead to fulminating congestive heart failure. Shift of sodium free intracellular fluid into the extracellular compartment following systemic absorption of solution may lower serum sodium concentration and aggravate pre-existing hyponatremia.

Care should be exercised if impaired liver function is known or suspected. Under such conditions, ammonia resulting from metabolism of glycine may accumulate in the blood.

Aseptic technique is essential with the use of sterile solutions for irrigation. The administration set should be attached promptly. Unused portions should be discarded and a fresh container of appropriate size used for the start-up of each cycle or repeat procedure.

Do not administer unless solution is clear, seal is intact and container is undamaged. Discard unused portion.

CARCINOGENESIS AND MUTAGENESIS AND IMPAIRMENT OF FERTILITY

Carcinogenesis, Mutagenesis, Impairment of Fertility: Studies with Glycine Irrigation, USP have not been performed to evaluate carcinogenic potential, mutagenic potential, or effects on fertility.

NURSING MOTHERS

Nursing Mothers: Caution should be exercised when Glycine Irrigation, USP is administered to a nursing woman.

Pregnancy: Teratogenic Effects.

Pregnancy Category C. Animal reproduction studies have not been conducted with Glycine Irrigation, USP. It is also not known whether Glycine Irrigation, USP can cause fetal harm when administered to a pregnant woman or can affect reproduction capacity. Glycine Irrigation, USP should be given to a pregnant woman only if clearly needed.

PEDIATRIC USE

Pediatric Use: The safety and effectiveness of Glycine Irrigation have not been established. Its limited use in pediatric patients has been inadequate to fully define proper dosage and limitations for use.

ADVERSE REACTIONS

Adverse reactions may result from intravascular absorption of glycine. Large intravenous doses of glycine are known to cause salivation, nausea and lightheadedness. Other consequences of absorption of urologic irrigating solutions include fluid and electrolyte disturbances such as acidosis, electrolyte loss, marked diuresis, urinary retention, edema, dryness of mouth, thirst, dehydration, coma from hyponatremia, secondary hyponatremia due to fluid overload, and hyperammonemia with resultant coma and/or encephalopathy; cardiovascular disorders such as hypotension, tachycardia, angina-like pains; pulmonary disorders such as pulmonary congestion; and other general reactions such as blurred vision, convulsions, nausea, vomiting, rhinitis, chills, vertigo, backache, transient blindness and urticaria. Allergic reactions from glycine are unknown or exceedingly rare.

Should any adverse reaction occur, discontinue the irrigant, evaluate the patient, institute appropriate therapeutic countermeasures and save the remainder of the fluid for examination if deemed necessary.

OVERDOSAGE

In the event of overhydration or solute overload, re-evaluate the patient and institute appropriate corrective measures. See WARNINGS, PRECAUTIONS and ADVERSE REACTIONS.

DOSAGE AND ADMINISTRATION

1.5% Glycine Irrigation, USP should be administered only by transurethral instillation with appropriate urologic instrumentation. A disposable irrigation set should be used. The total volume of solution used for irrigation is solely at the discretion of the surgeon.

Height of container(s) above the operating table in excess of 60 cm (approx. 2 ft.) has been reported to increase intravascular absorption of the irrigating fluid.

Drug Interactions

Additives may be incompatible. Consult with pharmacist, if available. When introducing additives, use aseptic technique, mix thoroughly and do not store.

Parenteral drug products should be inspected visually for particulate matter and discoloration prior to administration, whenever solution container permits. See PRECAUTIONS.

HOW SUPPLIED

1.5% Glycine Irrigation, USP is supplied in single-dose 3000 mL flexible irrigation container

NDC No. | Product | Container Size (mL)
0409-7974-08 | 1.5% Glycine Irrigation, USP | 3000 mL
0990-7974-08 | 1.5% Glycine Irrigation, USP | 3000 mL

ICU Medical is transitioning NDC codes from the "0409" to a "0990" labeler code. Both NDC codes are expected to be in the market for a period of time.

Exposure of pharmaceutical products to heat should be minimized. Avoid excessive heat. Protect from freezing. Store at 20 to 25°C (68 to 77°F). [See USP Controlled Room Temperature.]

Revised: November, 2022

ICU Medical, Inc., Lake Forest, Illinois, 60045, USA

IFU0000478

PRINCIPAL DISPLAY PANEL - 3000 mL Bag Label

3000 mL
NDC 0990-7974-08

1.5% GLYCINE
IRRIGATION, USP

EACH 100 mL CONTAINS GLYCINE
(AMINOACETIC ACID) 1.5 g.
pH 6.0 (4.5 TO 6.5)
200 mOsmol/LITER (CALC.)
STERILE, NONPYROGENIC,
HYPOTONIC.

INDICATIONS:
FOR UROLOGIC IRRIGATION.

CONTRAINDICATIONS:
NOT FOR INJECTION. USE ONLY IF
SOLUTION IS CLEAR AND
CONTAINER IS UNDAMAGED.

WARNINGS:
DO NOT HEAT OVER 66°C (150°F)
OR STORE ABOVE 40°C (104°F).
SINGLE-DOSE CONTAINER.
CONTAINS NO BACTERIOSTAT.
DISCARD UNUSED PORTION. USE
ASEPTIC TECHNIQUE.

USUAL DOSAGE:
SEE INSERT.

RX ONLY

3
V
CONTAINS DEHP

IM-4381

ICU Medical, Inc.,
Lake Forest, Illinois, 60045, USA

icumedical

PRINCIPAL DISPLAY PANEL - Overwrap Label

2
HDPE

TO OPEN TEAR AT NOTCH

DO NOT REMOVE FROM OVERWRAP UNTIL READY FOR USE. AFTER REMOVING
THE OVERWRAP, CHECK FOR MINUTE LEAKS BY SQUEEZING CONTAINER FIRMLY.
IF LEAKS ARE FOUND, DISCARD SOLUTION AS STERILITY MAY BE IMPAIRED.
RECOMMENDED STORAGE: ROOM TEMPERATURE (25°C). AVOID EXCESSIVE
HEAT. PROTECT FROM FREEZING. SEE INSERT.
98-4321-R14-3/98